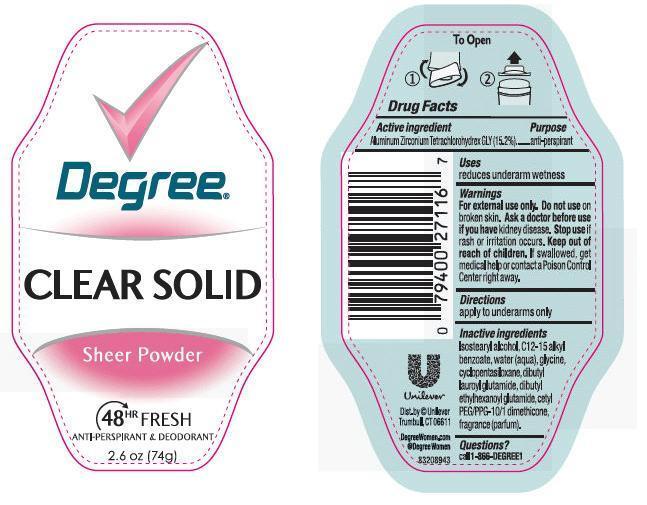 DRUG LABEL: Degree
NDC: 64942-1282 | Form: STICK
Manufacturer: Conopco Inc. d/b/a Unilever
Category: otc | Type: HUMAN OTC DRUG LABEL
Date: 20130117

ACTIVE INGREDIENTS: Aluminum Zirconium Tetrachlorohydrex GLY 15.2 g/100 g
INACTIVE INGREDIENTS: ISOSTEARYL ALCOHOL; ALKYL (C12-15) BENZOATE; WATER; GLYCINE; CYCLOMETHICONE 5; DIBUTYL LAUROYL GLUTAMIDE; DIBUTYL ETHYLHEXANOYL GLUTAMIDE; CETYL PEG/PPG-10/1 DIMETHICONE (HLB 5)

Degree Clear Solid Sheer Powder Antiperspirant deodorant

Active Ingredient

Aluminum Zirconium Tetrachlorohydrex GLY (15.2%)

Purpose
anti-perspirant

Uses

reduces underarm wetness

Warnings
For External Use Only

Do not use on broken skin

Ask a doctor before use if you have kidney disease

Stop use if rash or irritation occurs

Keep out of reach of children. If swallowed, get medical help or contact a Poison Control Center right away

Directions
apply to underarms only

Inactive ingredients
Isostearyl Alcohol, C12-15 Alkyl Benzoate, Water (Aqua), Glycine, Cyclopentasiloxane, Dibutyl Lauroyl Glutamide, Dibutyl Ethylhexanoyl Glutamide, Fragrance (Parfum), Cetyl PEG/PPG-10/1 Dimethicone

Questions? Call toll-free 1-800-866-DEGREE1